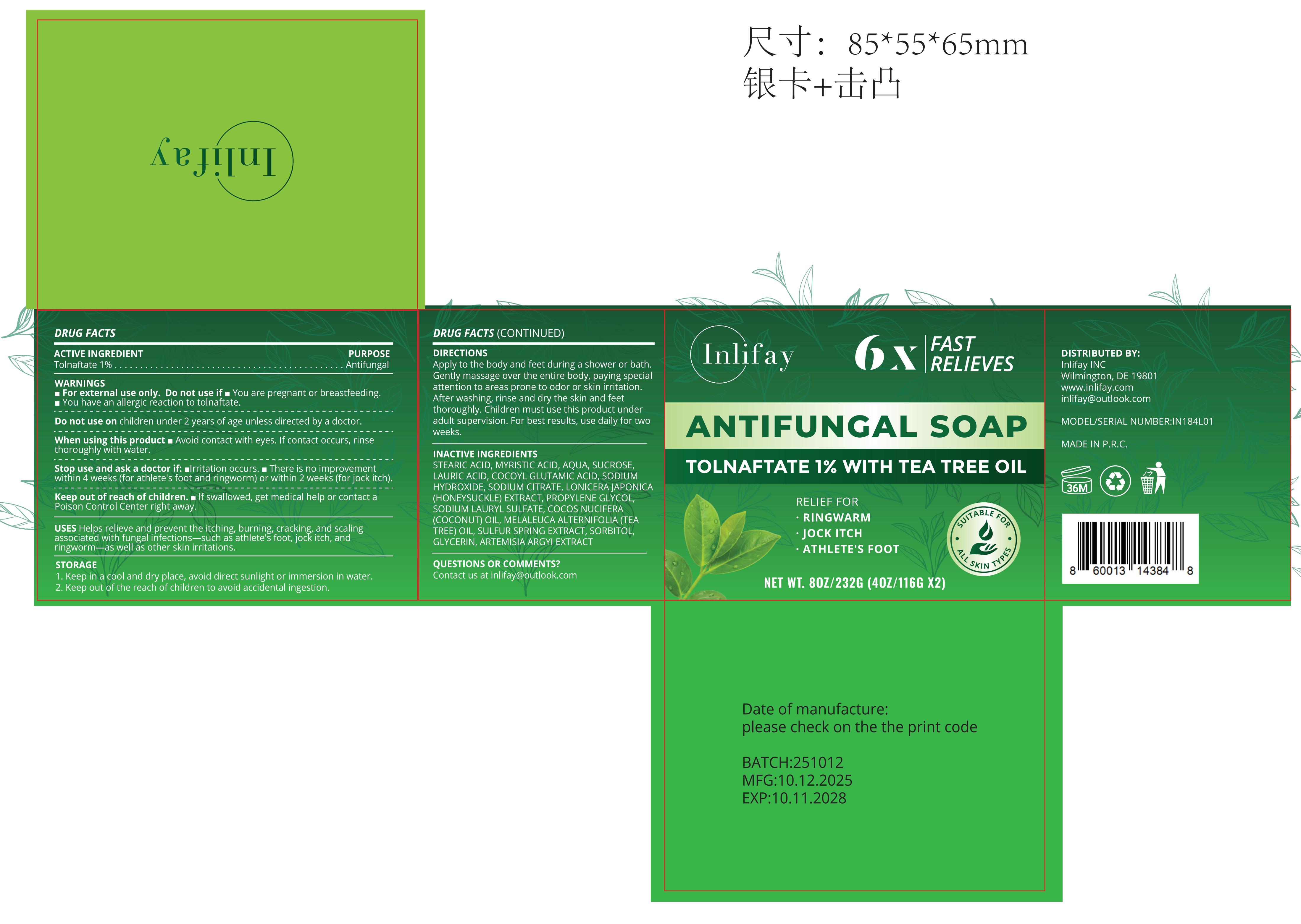 DRUG LABEL: Inlifay ANTIFUNGAL
NDC: 60771-0040 | Form: SOAP
Manufacturer: Guangzhou Haishi Biological Technology Co., Ltd.
Category: otc | Type: HUMAN OTC DRUG LABEL
Date: 20251016

ACTIVE INGREDIENTS: TOLNAFTATE 1 g/100 g
INACTIVE INGREDIENTS: SUCROSE; PROPYLENE GLYCOL; COCOS NUCIFERA (COCONUT) OIL; SORBITOL; GLYCERIN; MELALEUCA ALTERNIFOLIA (TEA TREE) LEAF OIL; LAURIC ACID; COCOYL GLUTAMIC ACID; SODIUM LAURYL SULFATE; SODIUM CITRATE; SULFUR; AQUA; STEARIC ACID; ARTEMISIA ARGYI LEAF; LONICERA JAPONICA FLOWER; MYRISTIC ACID; SODIUM HYDROXIDE

Inlifay ANTIFUNGAL SOAP

Active Ingredients

TOLNAFTATE 1%

Purpose

USES Helps relieve and prevent the itching, burning, cracking, and scalingassociated with fungal infections-such as athlete's foot, jock itch, andringworm-as well as other skin irritations.

Uses

Apply to the body and feet during a shower or bath.Gently massage over the entire body, paying specialattention to areas prone to odor or skin irritation.After washing, rinse and dry the skin and feetthoroughly. children must use this product underadult supervision. For best results, use daily for twoweeks.

Warnings

For external use only, Do not use if m You are pregnant or breastfeeding.
You have an allergic reaction to tolnaftate.

Stop Use

Stop use and ask a doctor if: mlrritation occurs

Do not use on children under 2 years of age unless directed by a doctor.

When Using

When using this product m Avoid contact with eyes. lf contact occurs, rinse thoroughw with water

Keep Out Of Reach Of Children

If swallowed, get medical help or contact a Poison Control Center right away.

Inactive ingredients

STEARIC ACID 26%
MYRISTIC ACID 12%
AQUA 10%
SUCROSE 10%
LAURIC ACID 8%
COCOYL GLUTAMIC ACID 8%
SODIUM HYDROXIDE 5%
SODIUM CITRATE 4%
LONICERA JAPONICA (HONEYSUCKLE) EXTRACT 3%

PROPYLENE GLYCOL 2%
SODIUM LAURYL SULFATE 2%
COCOS NUCIFERA (COCONUT) OIL 2%
MELALEUCA ALTERNIFOLIA (TEA TREE) OIL 2%
SULFUR SPRING EXTRACT 2%
SORBITOL 1%
GLYCERIN 1%
ARTEMISIA ARGYI EXTRACT 1%

Dosage & administration

Take an appropriate amount of soap, lather by rubbing, apply to the area to be cleaned, gently massage for 1-2 minutes, then rinse thoroughly with water